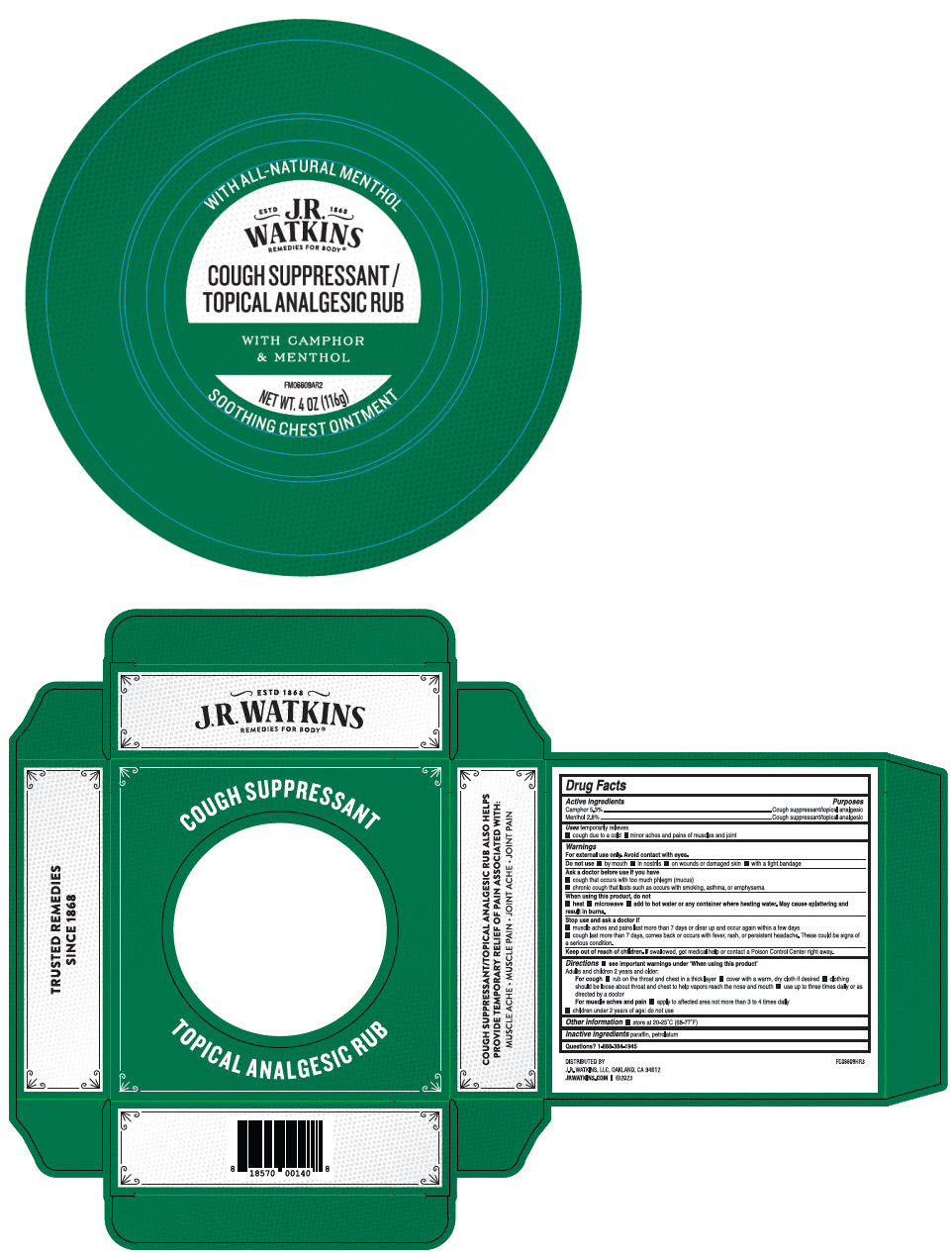 DRUG LABEL: Menthol Camphor Cough Suppressant Topical Analgesic Rub
NDC: 72342-220 | Form: OINTMENT
Manufacturer: J.R. Watkins, LLC.
Category: otc | Type: HUMAN OTC DRUG LABEL
Date: 20240208

ACTIVE INGREDIENTS: CAMPHOR (NATURAL) 5.3 g/100 g; MENTHOL, UNSPECIFIED FORM 2.8 g/100 g
INACTIVE INGREDIENTS: PARAFFIN; PETROLATUM

Menthol Camphor Cough Suppressant Topical Analgesic Rub

Drug Facts

ACTIVE INGREDIENT

Active Ingredients | Purpose
CAMPHOR 5.3% | Cough Suppressant/topical analgesic
MENTHOL 2.8% | Cough Suppressant/topical analgesic

Uses

temporarily relieves

- cough due to a cold
- minor aches and pains of muscles and joint

Warnings

For external use only. Avoid contact with eyes.

Do not use

- by mouth
- in nostrils
- on wounds or damaged skin
- with a tight bandage

Ask a doctor before use if you have

- cough that occurs with too much phlegm (mucus)
- chronic cough that lasts such as occurs with smoking, asthma, or emphysema

When using this product, do not

- heat
- microwave
- add to hot water or any container where heating water. May cause splattering and result in burns.

Stop use and ask a doctor if

- muscle aches and pains last more than 7 days or clear up and occur again within a few days
- cough last more than 7 days, comes back or occurs with fever, rash, or persistent headache. These could be signs of a serious condition.

Keep out of reach of children.If swallowed, get medical help or contact a Poison Control Center right away.

Directions

- see important warnings under 'When using this product'

Adults and children 2 years and older:

For cough

- rub on the throat and chest in a thick layer
- cover with a warm, dry cloth if desired
- clothing should be loose about throat and chest to help vapors reach the nose and mouth
- use up to three times daily or as directed by a doctor

For muscle aches and pain

- apply to affected area not more than 3 to 4 times daily
- children under 2 years of age: do not use

Other information

- store at 20-25°C (68-77°F)

Inactive ingredients

paraffin, petrolatum

Questions?

1-888-384-1945

DISTRIBUTED BY
J.R. WATKINS, LLC, OAKLAND, CA 94612

PRINCIPAL DISPLAY PANEL - 116 g Jar Box

COUGH SUPPRESSANT

WITH ALL-NATURAL MENTHOL

ESTD 1868
J.R.
WATKINS
REMEDIES FOR BODY®

COUGH SUPPRESSANT /
TOPICAL ANALGESIC RUB

WITH CAMPHOR
& MENTHOL

FM06609AR2

NET WT. 4 OZ (116g)

SOOTHING CHEST OINTMENT

TOPICAL ANALGESIC RUB